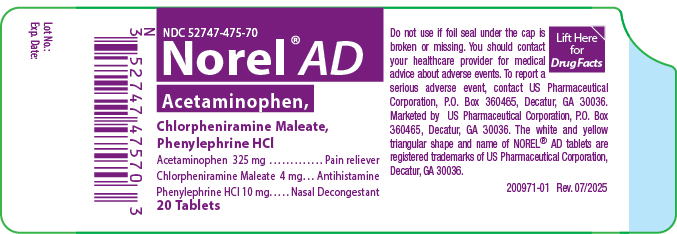 DRUG LABEL: Norel AD
NDC: 52747-475 | Form: TABLET, MULTILAYER
Manufacturer: U.S. PHARMACEUTICAL CORPORATION
Category: otc | Type: HUMAN OTC DRUG LABEL
Date: 20251017

ACTIVE INGREDIENTS: ACETAMINOPHEN 325 mg/1 1; CHLORPHENIRAMINE MALEATE 4 mg/1 1; PHENYLEPHRINE HYDROCHLORIDE 10 mg/1 1
INACTIVE INGREDIENTS: SILICON DIOXIDE; CROSPOVIDONE, UNSPECIFIED; MAGNESIUM STEARATE; MICROCRYSTALLINE CELLULOSE; POVIDONE K30; STARCH, CORN; STEARIC ACID; D&C YELLOW NO. 10; FD&C YELLOW NO. 6

Norel® AD

Active Ingredients (per tablet)

Acetaminophen 325 mg

Chlorpheniramine Maleate 4 mg

Phenylephrine HCl 10 mg

Purpose

Pain reliever

Antihistamine

Nasal decongestant

Uses

Temporarily relieves these symptoms due to the common cold or flu

- nasal congestion
- runny nose
- minor aches and pains
- headache
- sore throat
- sneezing
- itchy, watery eyes
- itching of the nose or throat
- sinus congestion and pressure
- temporarily reduces fever

Warnings

Liver warning:This product contains acetaminophen. Severe liver damage may occur if

- adult takes more than 6 tablets in 24 hours, which is the maximum daily amount
- child takes more than 5 doses in 24 hours
- taken with other drugs containing acetaminophen
- adult has 3 or more alcoholic drinks every day while using this product

Allergy alert:Acetaminophen may cause severe skin reaction.
Symptoms may include:

- skin reddening
- blisters
- rash

If a skin reaction occurs, stop use and seek medical help right away.

Sore throat warning:If sore throat is severe, persists for more than 2 days, is accompanied or followed by fever, headache, rash, nausea or vomiting, speak with a healthcare provider.

Do not use

- with any other drug containing acetaminophen (prescription or nonprescription). If you are not sure whether a drug contains acetaminophen, ask a doctor or pharmacist.
- if you are now taking a prescription monoamine oxidase inhibitor (MAOI) (certain drugs for depression, psychiatric, or emotional conditions, or Parkinson's disease), or for 2 weeks after stopping the MAOI drug. If you do not know if your prescription drug contains an MAOI, ask a doctor or pharmacist before taking this product

Ask a doctor before use if you have

- liver disease
- heart disease
- high blood pressure
- thyroid disease
- diabetes
- glaucoma
- trouble urinating due to an enlarged prostate gland
- a breathing problem such as emphysema or chronic bronchitis

Ask a doctor or pharmacist before use if you are

- taking the blood thinning drug warfarin
- taking any other nasal decongestant or stimulant
- taking sedatives or tranquilizers

When using this product

- do not exceed recommended dosage
- drowsiness may occur
- avoid alcoholic beverages
- alcohol, sedatives, and tranquilizers may increase drowsiness
- be careful when driving a motor vehicle or operating machinery
- excitability may occur, especially in children

Stop use and ask a doctor if

- pain or nasal congestion gets worse or lasts more than 7 days
- fever gets worse or lasts more than 3 days
- redness or swelling is present
- you get nervous, dizzy, or sleepless
- new symptoms occur

If pregnant or breast feeding

- ask a health professional before use

Keep out of the reach of children.

Taking more than the recommended dose can cause serious health problems. In case of overdose, get medical help or contact Poison Control Center right away. Quick medical attention is critical for adults as well as for children even if you do not notice any signs or symptoms.

Directions

- do not take more than directed (see overdose warning)
- adults and children 12 years of age and over: take 1 tablet every 4 hours, while symptoms persist
- do not take more than 6 tablets in 24 hours, unless directed by a doctor
- children under 12 years of age: ask a doctor

Other Information

store at 20°-25°C (68°-77°F)

Overdose Warning:Keep this and all medication out of the reach of children. In case of accidental overdose, seek medical help or contact a Poison Control Center immediately.

Inactive Ingredients

Colloidal Silicon Dioxide, Crospovidone Polyplasdone, Magnesium Stearate (vegetable base), Microcrystalline Cellulose, Povidone K-30, Pregelatinized Starch, Stearic Acid, D&C Yellow #10, FD&C Yellow #6.

Questions or Comments

Please visit www.uspco.comor contact us at US Pharmaceutical Corporation, P.O. Box 360465, Decatur, GA 30036

Principal Display Panel

Figure 1:Norel®AD container label